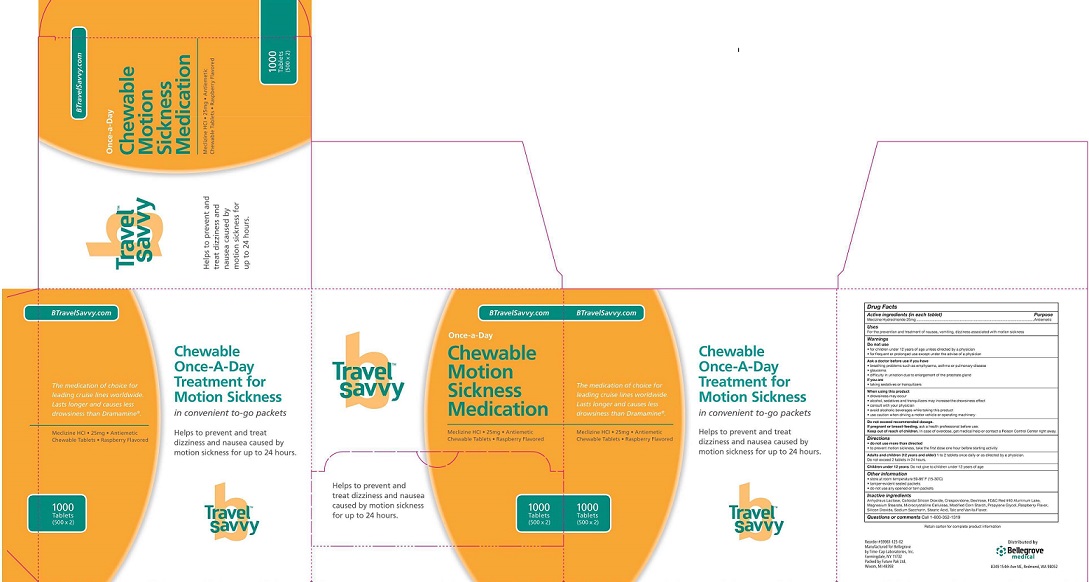 DRUG LABEL: meclinzine hydorchloride
NDC: 59961-125 | Form: TABLET, CHEWABLE
Manufacturer: Bellegrove Medical Supply, Inc.
Category: otc | Type: HUMAN OTC DRUG LABEL
Date: 20201102

ACTIVE INGREDIENTS: Meclizine hydrochloride 25 mg/1 1
INACTIVE INGREDIENTS: anhydrous lactose 1 mg/1 1

Meclizine Hydrochloride - Chewable

Do not use
• for children under 12 years of age unless unless directed by a physician
• for frequent or prolonged use except under the advice of a physician

Ask a doctor before use if you have

breathing problems such as emphysema, asthma or pulmonary disease
glaucoma

if you are

- taking sedatives or tranquilizers

When using this product

drowsiness may occur
alcohol, sedatives and tranquilizers may increase the drowsiness effect
consult with your physician
avoid alcoholic beverages while taking this product
use caution when driving a motor vehicle or operating machinery

Do not exceed recommended dosage

If preganant or breast-feeding, ask a health professional before use

Keep out of reach of children. In case of overdose, get medical help or contact Poison Control Center right away

Other information

- store at room temperature 59-86 degrees F (15-30 degreesC)
- tamper-evident sealed packets
- do not use any opened or torn packets

DOSAGE AND ADMINISTAATION

Directions

do not use more than directed
to provent motion sickness, take the first dose one hour before starting activity
Adults and children (12 years and older)

1 to 2 tablets once daily or as directed by a Physician

Do not exceed 2 tablets in 24 hours

Children under 12 years of age: Do not give to children under 12 years of age

INDICATION AND USAGE

For the prevention and treatment of the nausea,vomating,or dizziness associated with motion sickness.

OTC-KEEP OUT OF REACH OF CHILDREN

Do not use
• for children under 12 years of age unless unless directed by a physician
Keep out of reach of children. In case of overdose, get medical help or contact Poison Control Center right away

PURPOSE

When using this product

drowsiness may occur
alcohol, sedatives and tranquilizers may increase the drowsiness effect
consult with your physician
avoid alcoholic beverages while taking this product
use caution when driving a motor vehicle or operating machinery

Active ingredients

anhydrous lactose

Inactive ingredients

Anhydrous Lactose, Colloidal Silicon Dioxide, Crospovidone, Dextrose, FD&C red #40 aluminum lake, magnesium stearate, Microcrystalline Cellulose, Modified Corn Starch, Propylene Glycol, Raspberry Flavor, Silicon Dioxide, Sodium Saccharin, Stearic Acid, Talc and Vanilla Flavor.